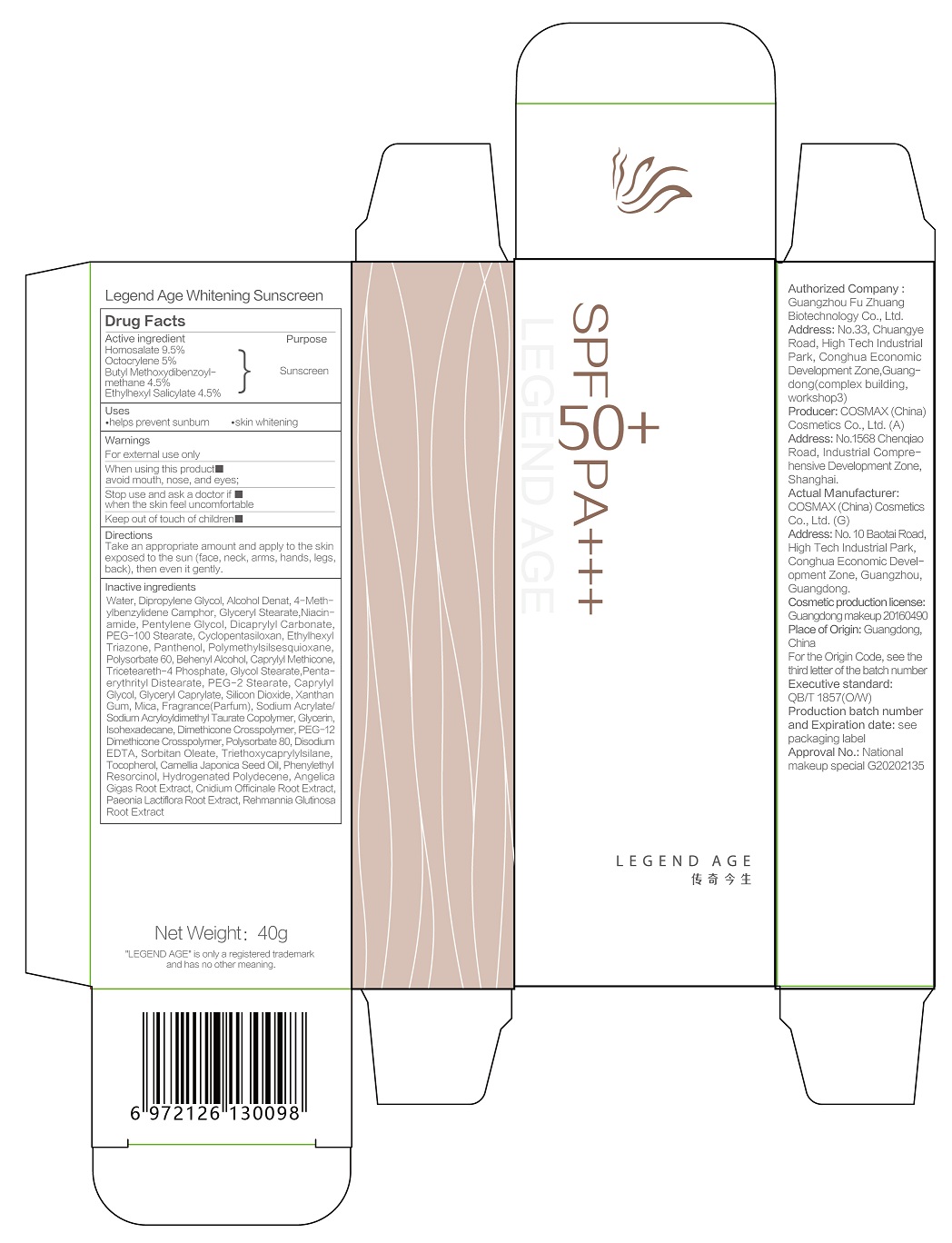 DRUG LABEL: Legend Age Whitening Sunscreen
NDC: 82142-001 | Form: CREAM
Manufacturer: Guangzhou Fu Zhuang Biotechnology Co.,Ltd.
Category: otc | Type: HUMAN OTC DRUG LABEL
Date: 20210623

ACTIVE INGREDIENTS: HOMOSALATE 9.5 g/100 g; OCTOCRYLENE 5 g/100 g; AVOBENZONE 4.5 g/100 g; OCTISALATE 4.5 g/100 g
INACTIVE INGREDIENTS: POLYMETHYLSILSESQUIOXANE (4.5 MICRONS); HYDROGENATED POLYDECENE (1500 CST); NIACINAMIDE; POLYSORBATE 80; TRIETHOXYCAPRYLYLSILANE; TOCOPHEROL; CAMELLIA JAPONICA SEED OIL; SORBITAN MONOOLEATE; EDETATE DISODIUM ANHYDROUS; ALCOHOL; GLYCERYL MONOSTEARATE; CYCLOMETHICONE 5; DIPROPYLENE GLYCOL; XANTHAN GUM; MICA; POLYSORBATE 60; PENTAERYTHRITYL DISTEARATE; ENZACAMENE; PENTYLENE GLYCOL; DICAPRYLYL CARBONATE; ETHYLHEXYL TRIAZONE; TRICETEARETH-4 PHOSPHATE; GLYCOL STEARATE; DOCOSANOL; WATER; PEG-100 STEARATE; PANTHENOL; PEG-2 STEARATE; CAPRYLYL GLYCOL; GLYCERYL CAPRYLATE; SODIUM ACRYLATE/SODIUM ACRYLOYLDIMETHYLTAURATE COPOLYMER (4000000 MW); GLYCERIN; ISOHEXADECANE; DIMETHICONE CROSSPOLYMER (450000 MPA.S AT 12% IN CYCLOPENTASILOXANE); PEG-12 DIMETHICONE/PPG-20 CROSSPOLYMER; ANGELICA GIGAS ROOT; CNIDIUM OFFICINALE ROOT; PHENYLETHYL RESORCINOL; PAEONIA LACTIFLORA ROOT; REHMANNIA GLUTINOSA ROOT; SILICON DIOXIDE

WARNINGS

- For external use only
- When using this product, avoid mouth, nose and eyes
- Stop use and ask a doctor if when the skin feels uncomfortable
- Keep out of touch of children

- Keep out of touch of children.

INACTIVE INGREDIENT

Water, Dipropylene Glycol, Alcohol Denat, 4-Methylbenzylidene Camphor, Glyceryl Stearate, Niacinamide, Pentylene Glycol, Dicaprylyl Carbonate, PEG-100 Stearate, Cyclopentasiloxan, Ethylhexyl Triazone, Panthenol, Polymethylsilsesquioxane, Polysorbate 60, Behenyl Alcohol, Caprylyl Methicone, Triceteareth-4 Phosphate, Glycol Stearate, Pentaerythrityl Distearate, PEG-2 Stearate, Caprylyl Glycol, Glyceryl Caprylate, Silicon Dioxide, Xanthan Gum, Mica, Fragrance(Parfum), Sodium Acrylate/Sodium Acryloyldimethyl Taurate Copolymer, Glycerin, Isohexadecane, Dimethicone Crosspolymer, PEG-12 Dimethicone Crosspolymer, Polysorbate 80, Disodium EDTA, Sorbitan Oleate, Triethoxycaprylylsilane, Tocopherol, Camellia Japonica Seed Oil, Phenylethyl Resorcinol, Hydrogenated Polydecene, Angelica Gigas Root Extract, Cnidium Officinale Root Extract, Paeonia Lactiflora Root Extract, Rehmannia Glutinosa Root Extract

ACTIVE INGREDIENT

Homosalate 9.5%

Octocrylene 5%

Butyl Methoxydibenzoylmethane 4.5%

Ethylhexyl Salicylate 4.5%

PURPOSE

- helps prevent sunburn
- skin whitening

DOSAGE AND ADMINISTRATION

Take an appropriate amount and apply to the skin exposed to the sun (face, neck, arms, hands, legs, back), then even it gently.

INDICATIONS AND USAGE

Take an appropriate amount and apply to the skin exposed to the sun (face, neck, arms, hands, legs, back), then even it gently.